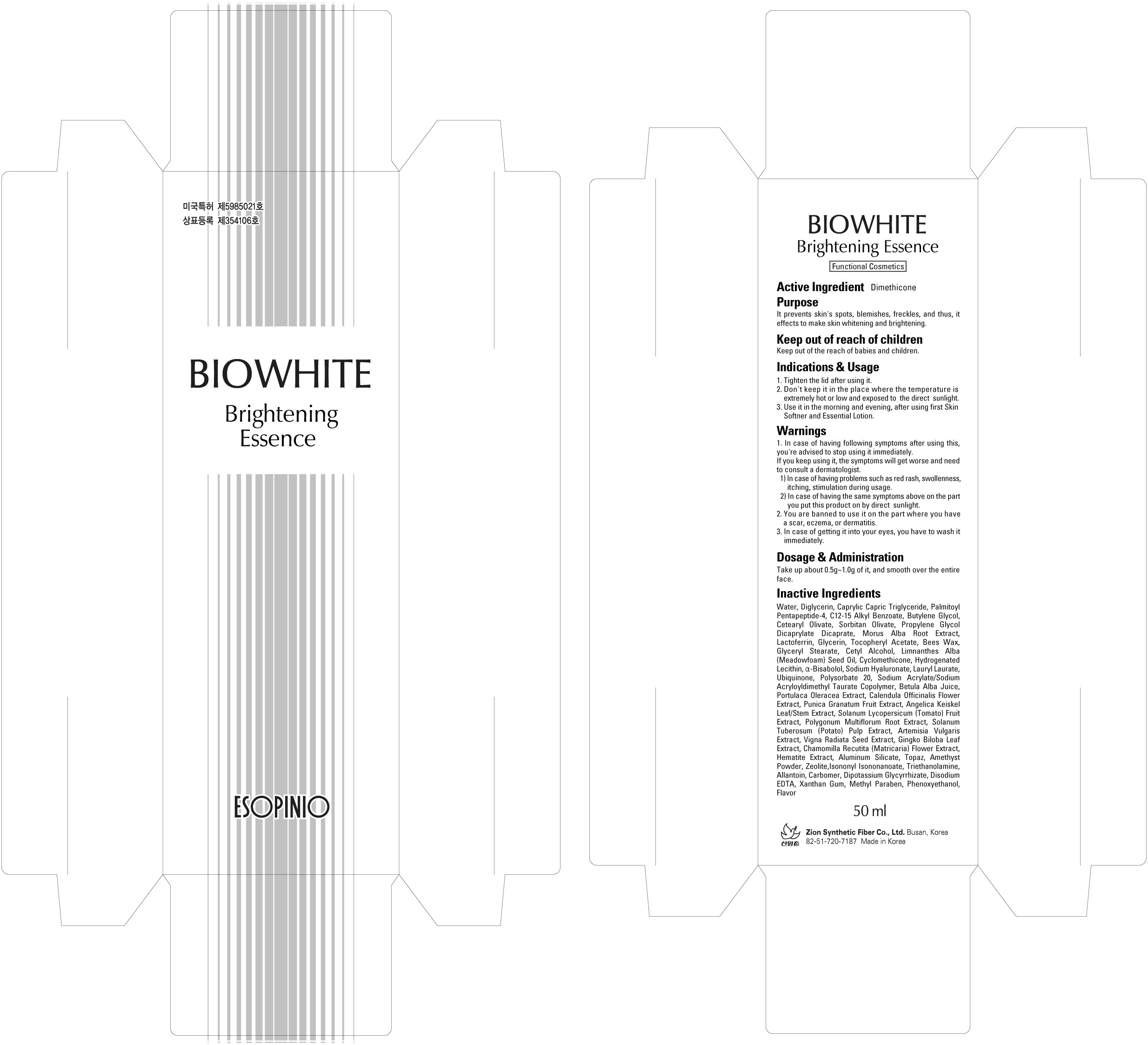 DRUG LABEL: BIOWHITE BRIGHTENING
NDC: 44781-160 | Form: CREAM
Manufacturer: ZION SYNTHETIC FIBER CO., LTD.
Category: otc | Type: HUMAN OTC DRUG LABEL
Date: 20110422

ACTIVE INGREDIENTS: DIMETHICONE 0.5 mL/50 mL
INACTIVE INGREDIENTS: Water; Butylene Glycol; Glycerin; GLYCERYL MONOSTEARATE; Cetyl Alcohol

Drug Facts

Active Ingredient: DIMETHICONE

Inactive Ingredients:
Water, Diglycerin, Caprylic Capric Triglyceride, Palmitoyl Pentapeptide-4, C12-15 Alkyl Benzoate, Butylene Glycol, Cetearyl Olivate, Sorbitan Olivate, Propylene Glycol Dicaprylate Dicaprate, Morus Alba Root Extract, Lactoferrin, Glycerin, Tocopheryl Acetate, Beeswax, Glyceryl Stearate, Cetyl Alcohol, Limnanthes Alba (Meadowfoam)Seed Oil, Cyclomethicone, Hydrogenated Lecithin, Alpha-Bisabolol, Sodium Hyaluronate, Lauryl Laurate, Ubiquinone, Polysorbate 20, Sodium Acrylate/Sodium Acryloyldimethyl Taurate Copolymer, Betula Alba Juice, Portulaca Oleracea extract, Calendula Officinalis Flower Extact, Punica Granatum Fruit Extract, Angelica Keiskei Leaf/Stem Extract, Solanum Lycopersicum (Tomato) Fruit Extract, Polygonum Multiflorum Root Extract, Solanum Tuberosum (Potato) Pulp Extract, Artemisia Vulgaris Extract, Vigna Radiata Seed Extract, Gingko Biloba Leaf Extract, Chamomilla Recutita (Matricaria) Flower Extract,
Hematite Extract, Aluminum Silicate, Topaz, Amethyst Powder, Zeolite, Isononyl Isononanoate, Triethanolamine, Allantoin, Carbomer, Dipotassium Glycyrrhizate, Disodium EDTA, Xanthan Gum, Methyl Paraben, Phenoxyethanol, Flavor

Purpose:
It prevents skin's spots, blemishes, freckles, and thus, it effects to make skin whitening and brightening.

Warnings:
In case of having following symptoms after using this, you're advised to stop using it immediately. If you keep using it, the symptoms will get worse and need to consult a dermatologist.
- In case of having problems such as red rash, swollenness, itching, stimulation during usage.
- In case of having the same symptoms above on the part you put this product on by direct sunlight.
You are banned to use it on the part where you have a scar, eczema, or dermatitis.
In case of getting it into your eyes, you have to wash it immediately.

Keep out of reach of children:
Keep out of the reach of babies and children.

Indication and usage:
Tighten the lid after using it.
Don't keep it in the place where the temperature is extremely hot or low and exposed to the direct sunlight.
Use it in the morning and evening, after using first Skin Softner and Essential Lotion.

Dosage and administration:
Take up about 0.5g - 1.0g of it, and smooth over the entire face.